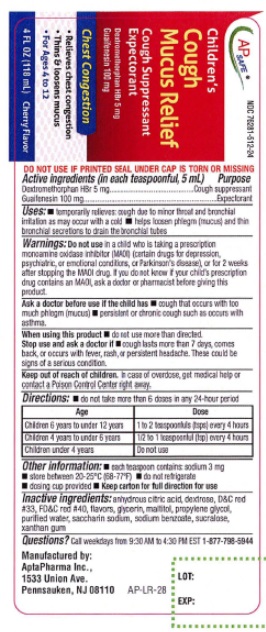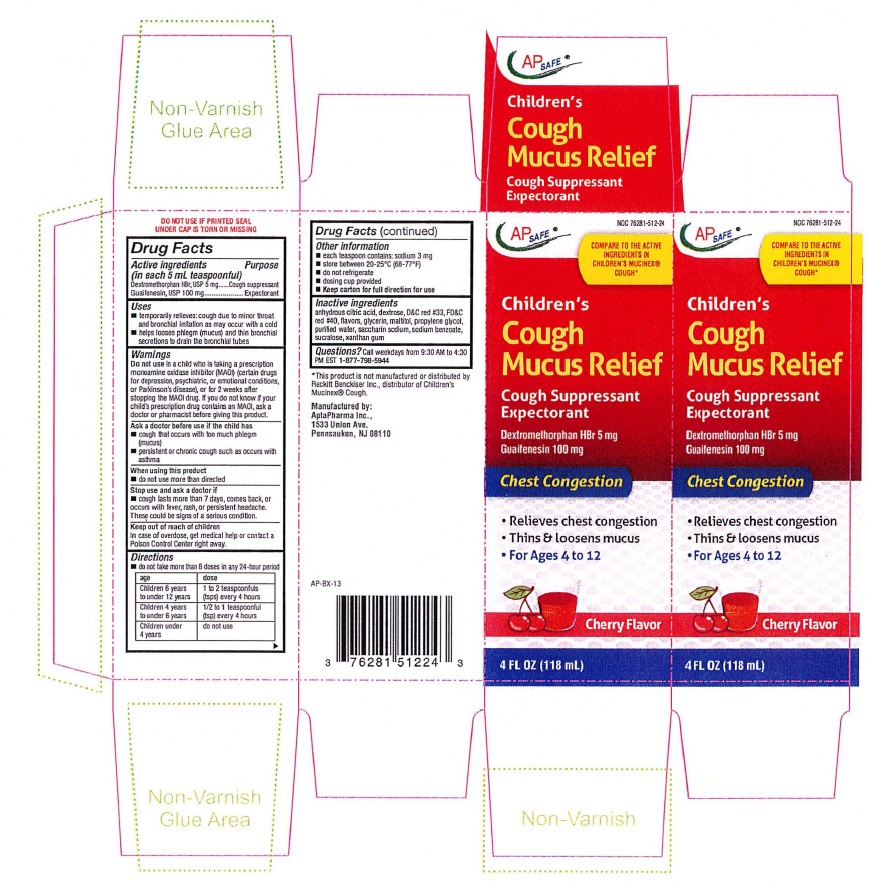 DRUG LABEL: CHILDRENS MUCUS RELIEF COUGH - CHERRY FLAVOR
NDC: 76281-512 | Form: LIQUID
Manufacturer: AptaPharma Inc.
Category: otc | Type: HUMAN OTC DRUG LABEL
Date: 20251226

ACTIVE INGREDIENTS: DEXTROMETHORPHAN HYDROBROMIDE 5 mg/5 mL; GUAIFENESIN 100 mg/5 mL
INACTIVE INGREDIENTS: ANHYDROUS CITRIC ACID; DEXTROSE; D&C RED NO. 33; FD&C RED NO. 40; GLYCERIN; MALTITOL; PROPYLENE GLYCOL; WATER; SACCHARIN SODIUM; SODIUM BENZOATE; SUCRALOSE; XANTHAN GUM

CHILDREN'S MUCUS RELIEF COUGH - CHERRY FLAVOR

DRUG FACTS

Active ingredients
(in each 5 mL teaspoonful)
Dextromethorphan HBr, USP 5 mg
Guaifenesin, USP 100 mg

Purpose
Dextromelhorphan HBr, USP ....... Cough Suppressant
Guaifenestn,USP ........................Expectorant

Uses

• temporarily relieves:cough due to minor throat and bronchial irritation as may occur with a cold

• helps loosen phlegm (mucus) and thin bronchial secretions to drain the bronchial tube

Warnings
Do not use ina child who is taking a prescription monoamine oxidase inhibitor (MAOI) (certain
drugs for depression, psychiatric, or emotional conditions, or Parkinson' s disease), or for 2
weeks after stopping the MAOI drug. If you do not know if your child's prescription drug
contains an MAOI, ask a doctor or pharmacist before giving this product.

Ask a doctor before use if the child has
• cough that occurs with too much phlegm (mucus)
• persistent or chronic cough such as occurs with asthma

When using this product•do not use more than directed

Stop use and ask a doctor if
• cough lasts more than 7 days, comes back, or occurs with fever, rash, or persistent headache.
These could be signs of a serious condition.

Keep out of reach of children.In case of overdose, get
medical help or contact a Poison Control Center right
away.

Directions
•do not take more than 6 doses in any 24-hour period

Age Dose

Children 6 years to Under 12 years | 1 to 2 teaspoonfuls (tsps) every 4 hours
Children 4 years to Under 6 years | 1/2 to 1 teaspoonful (tsp) every 4 hours
Children under 4 years | do not use

Other information• each teaspoon contains: sodium 3 mg

•store between 20-25°C (68-77°F) •do not refrigerate

•dosing cup provided • Keep carton for full direction for use

INACTIVE INGREDIENT

Inactive ingredients:anhydrous citric acid, dextrose, D&C red
#33, FD&C red #40, flavors, glycerin, maltitol, propylene glycol,
purified water, saccharin sodium, sodium benzoate, sucralose,
xanthan gum

QUESTIONS

Questions?Call weekdays from 9:30AM to 4:30 PM EST 1-877-798-5944

CHILDREN'S MUCUS RELIEF COUGH CHERRY

AP SAFE NDC 76281-512-24

Children's
Cough
Mucus Relief

Cough Suppressant
Expectorant

Cherry Flavor
4 FL OZ (118 mL)

DO NOT USE IF PRINTED SEAL UNDER CAP IS TORN OR MISSING

*This product is not manufactured or distributed by
Reckitt Benckiser Inc., distributor of Children's
Mucinex®Cough.

Manufactured by:
AptaPharma Inc.,
1533 Union Ave.
Pennsauken, NJ 08110

res